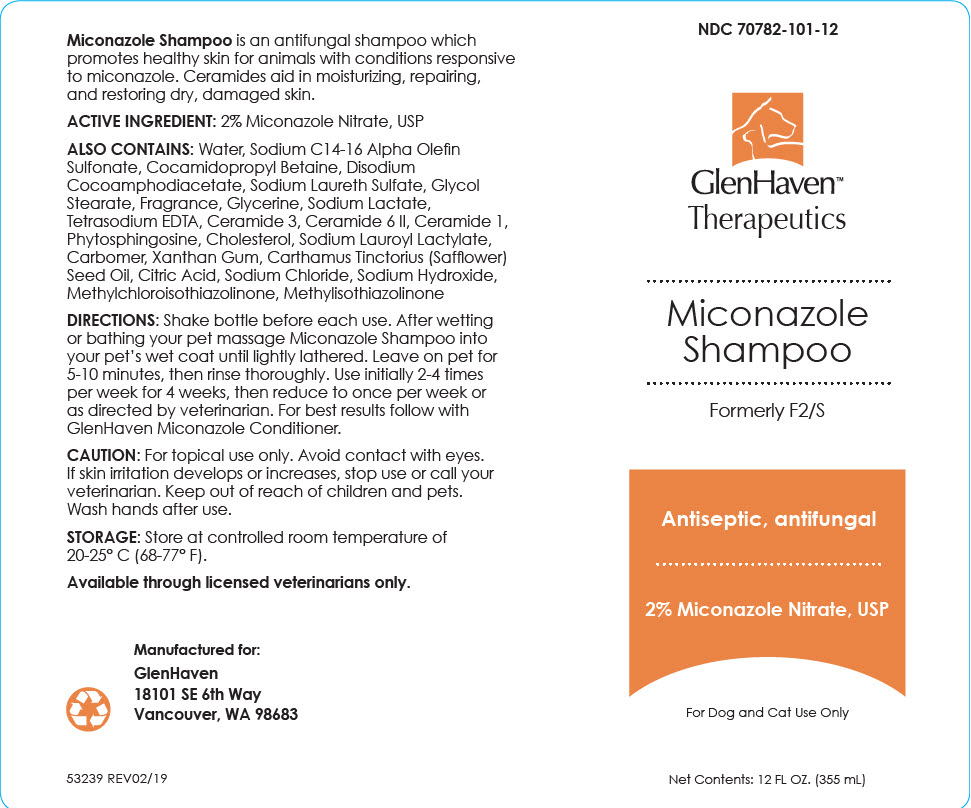 DRUG LABEL: Miconazole
NDC: 70782-101 | Form: SHAMPOO
Manufacturer: GlenHaven LLC
Category: animal | Type: OTC ANIMAL DRUG LABEL
Date: 20211207

ACTIVE INGREDIENTS: Miconazole Nitrate 20 mg/1 mL

Miconazole Shampoo

VETERINARY INDICATIONS

Miconazole Shampoo is an antifungal shampoo which promotes healthy skin for animals with conditions responsive to miconazole. Ceramides aid in moisturizing, repairing, and restoring dry, damaged skin.

ACTIVE INGREDIENT: 2% Miconazole Nitrate, USP

DESCRIPTION

ALSO CONTAINS: Water, Sodium C14-16 Alpha Olefin Sulfonate, Cocamidopropyl Betaine, Disodium Cocoamphodiacetate, Sodium Laureth Sulfate, Glycol Stearate, Fragrance, Glycerine, Sodium Lactate, Tetrasodium EDTA, Ceramide 3, Ceramide 6 II, Ceramide 1, Phytosphingosine, Cholesterol, Sodium Lauroyl Lactylate, Carbomer, Xanthan Gum, Carthamus Tinctorius (Safflower) Seed Oil, Citric Acid, Sodium Chloride, Sodium Hydroxide, Methylchloroisothiazolinone, Methylisothiazolinone

DOSAGE AND ADMINISTRATION

DIRECTIONS: Shake bottle before each use. After wetting or bathing your pet massage Miconazole Shampoo into your pet's wet coat until lightly lathered. Leave on pet for 5-10 minutes, then rinse thoroughly. Use initially 2-4 times per week for 4 weeks, then reduce to once per week or as directed by veterinarian. For best results follow with GlenHaven Miconazole Conditioner.

SAFE HANDLING WARNING

CAUTION: For topical use only. Avoid contact with eyes. If skin irritation develops or increases, stop use or call your veterinarian. Keep out of reach of children and pets. Wash hands after use.

STORAGE AND HANDLING

STORAGE: Store at controlled room temperature of 20-25° C (68-77° F).

INFORMATION FOR OWNERS/CAREGIVERS

Available through licensed veterinarians only.

Manufactured for:

GlenHaven
18101 SE 6th Way
Vancouver, WA 98683

53239 REV02/19

PRINCIPAL DISPLAY PANEL - 355 mL Bottle Label

NDC 70782-101-12

GlenHaven™
Therapeutics

Miconazole
Shampoo

Formerly F2/S

Antiseptic, antifungal

2% Miconazole Nitrate, USP

For Dog and Cat Use Only

Net Contents: 12 FL OZ. (355 mL)